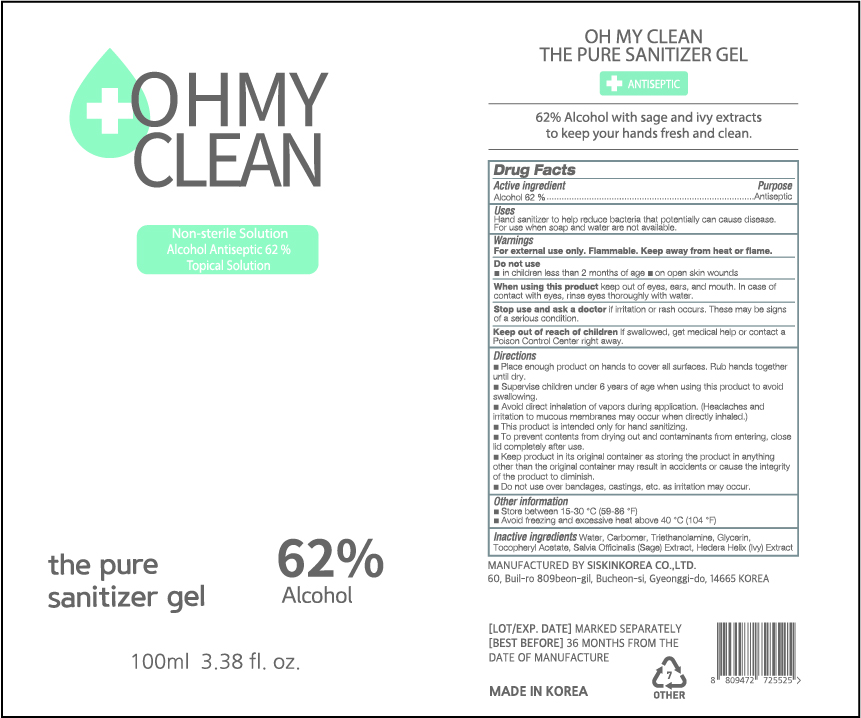 DRUG LABEL: OH MY CLEAN THE PURE SANITIZER Gel
NDC: 74514-1062 | Form: GEL
Manufacturer: SISKINKOREA CO.,LTD.
Category: otc | Type: HUMAN OTC DRUG LABEL
Date: 20200514

ACTIVE INGREDIENTS: ALCOHOL 62 mL/100 mL
INACTIVE INGREDIENTS: TROLAMINE; GLYCERIN; .ALPHA.-TOCOPHEROL ACETATE; SAGE; WATER; HEDERA HELIX LEAF; CARBOMER HOMOPOLYMER, UNSPECIFIED TYPE

Packaging change 100ml_62%_gel_OH MY CLEAN THE PURE SANITIZER GEL [74514-0162-1]-> 74514-1062-1